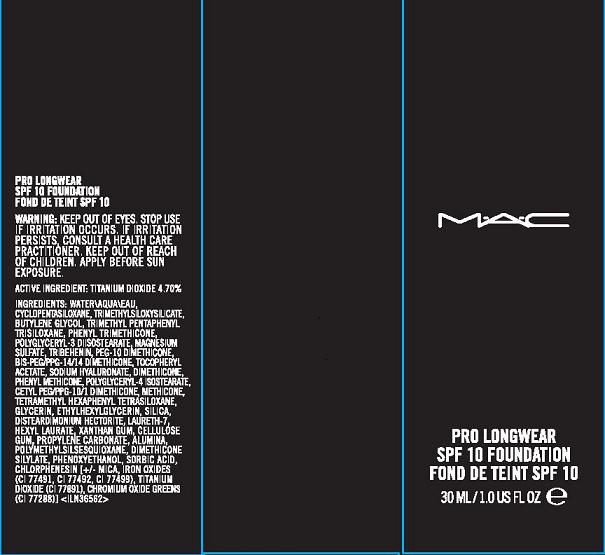 DRUG LABEL: PRO-LONGWEAR
NDC: 40046-0038 | Form: LOTION
Manufacturer: MAKE UP ART COSMETICS
Category: otc | Type: HUMAN OTC DRUG LABEL
Date: 20100824

ACTIVE INGREDIENTS: TITANIUM DIOXIDE 4.7 mL/100 mL

ACTIVE INGREDIENT: TITANIUM DIOXIDE, 4.7%

WARNINGS

WARNINGS: KEEP OUT OF EYES. STOP USE IF IRRITATION OCCURS. IF IRRITATION PERSISTS, CONSULT A HEATH CARE PRACTITIONER. KEEP OUT OF REACH OF CHILDREN. APPLY BEFORE SUN EXPOSURE

PACKAGE LABEL

MAC

PRO LONGWEAR

SPF 10

FOUNDATION

30 ML/1.0 OZ US FL
MAKE UP ART COSMETICS
NEW YORK, NY